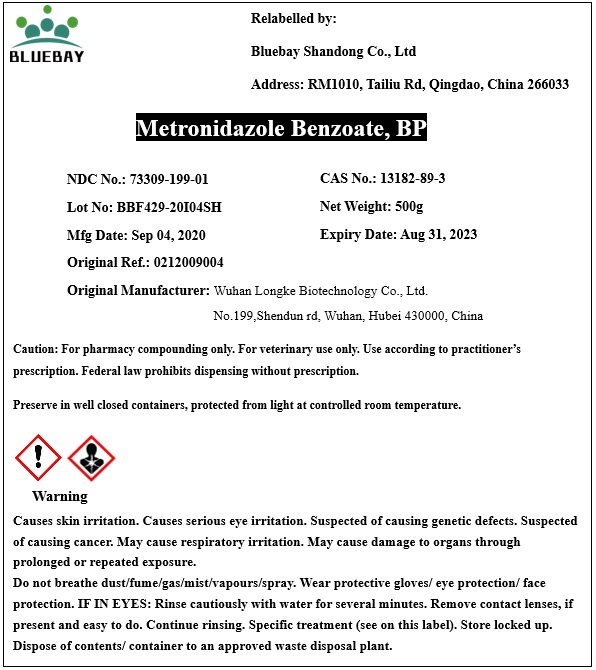 DRUG LABEL: Metronidazole Benzoate
NDC: 73309-199 | Form: POWDER
Manufacturer: BLUEBAY SHANDONG CO.,LTD
Category: other | Type: BULK INGREDIENT
Date: 20200930

ACTIVE INGREDIENTS: METRONIDAZOLE BENZOATE 1 g/1 g

Metronidazole Benzoate